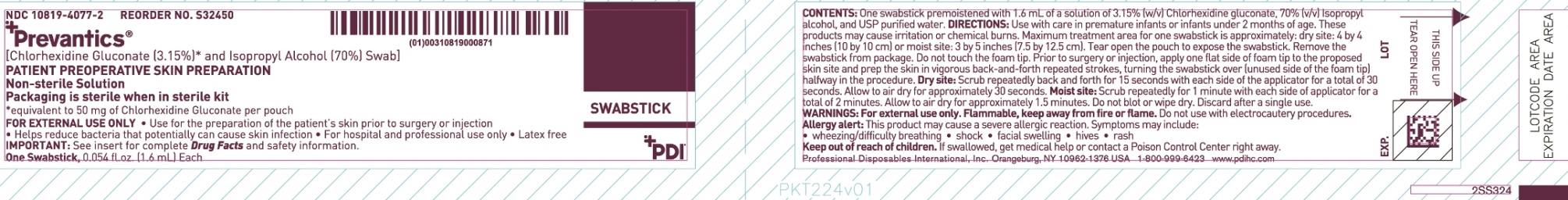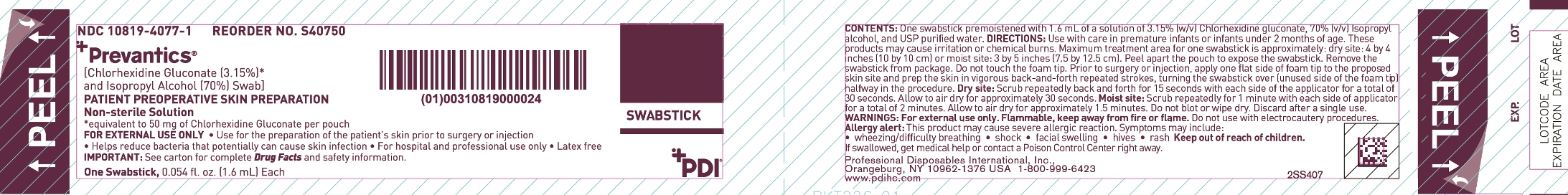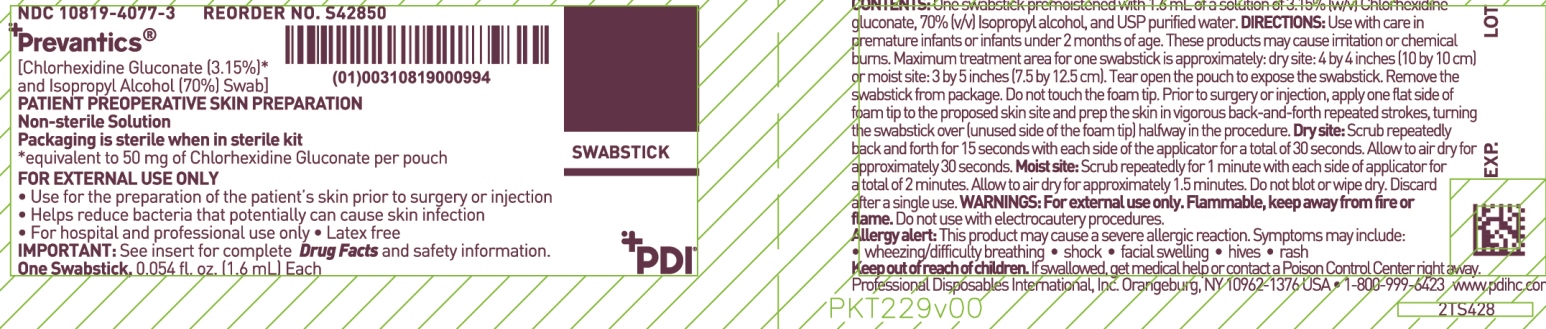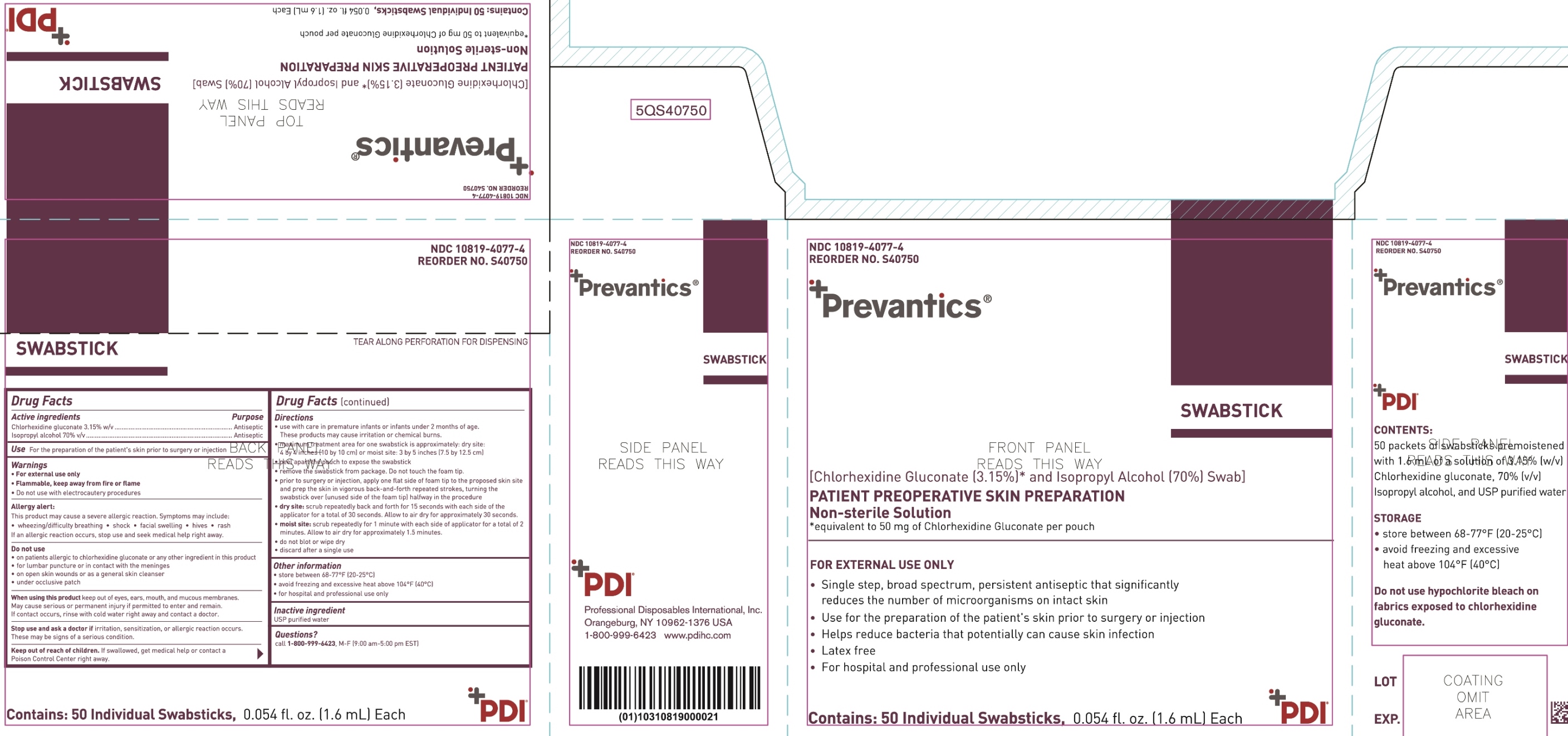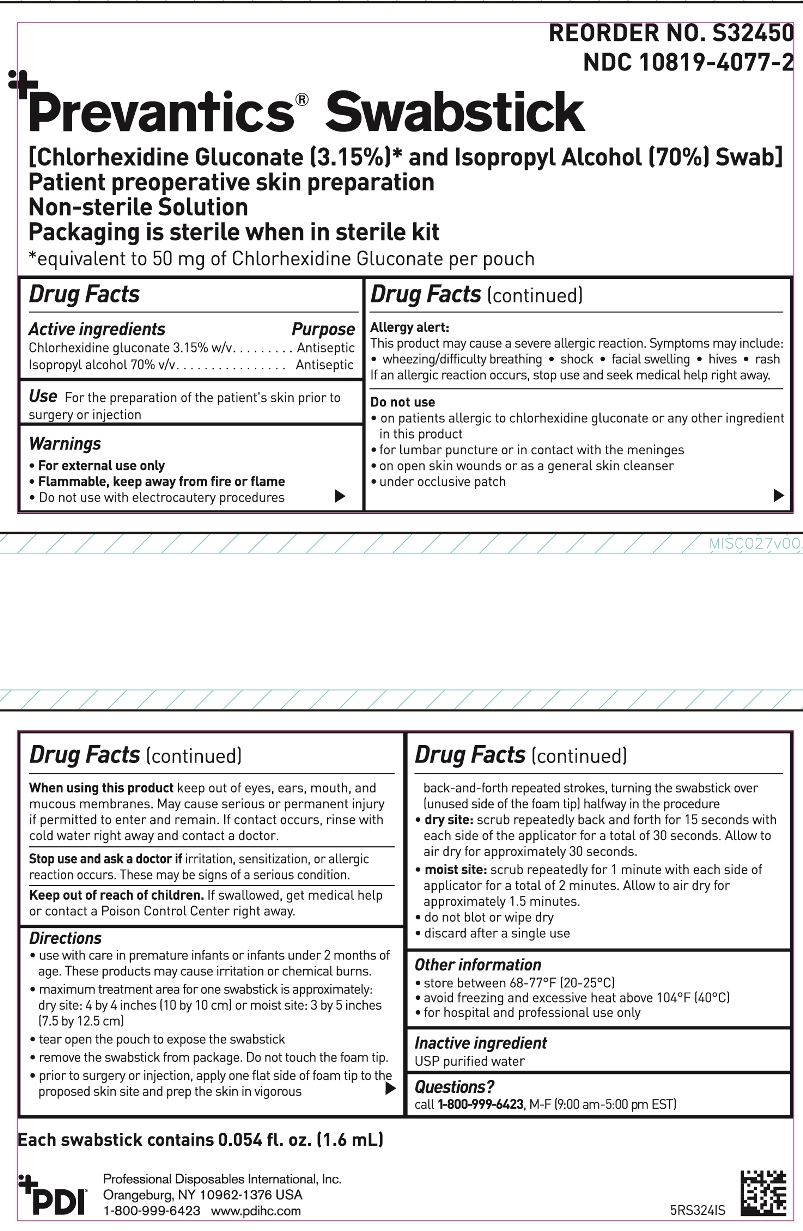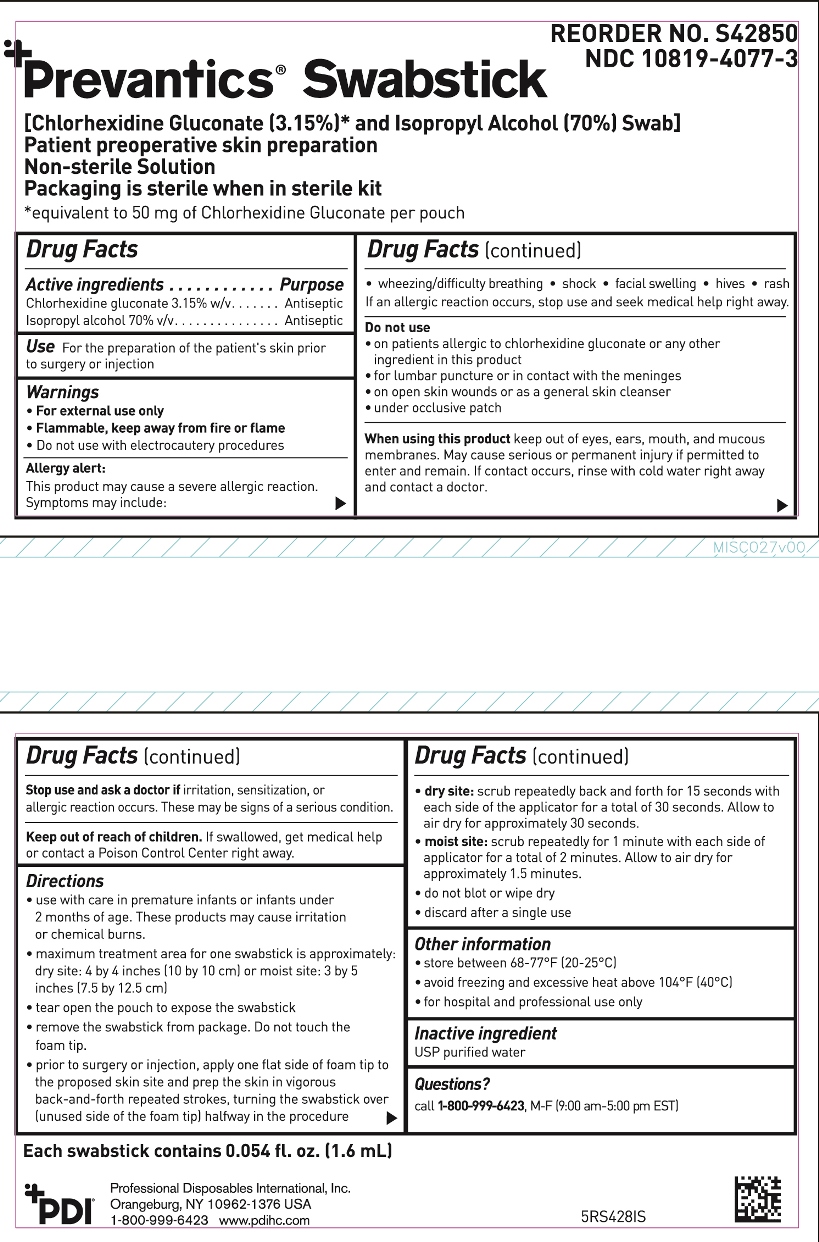 DRUG LABEL: Prevantics Swabstick
NDC: 10819-4077 | Form: SOLUTION
Manufacturer: Professional Disposables International, Inc.
Category: otc | Type: HUMAN OTC DRUG LABEL
Date: 20250210

ACTIVE INGREDIENTS: CHLORHEXIDINE GLUCONATE 31.5 mg/1 mL; ISOPROPYL ALCOHOL 0.7 mL/1 mL
INACTIVE INGREDIENTS: WATER

S40750- NDC 10819-4077-1
S40750- NDC 10819-4077-4
S32450- NDC 10819-4077-2
S42850- NDC 10819-4077-3

Active ingredients

Chlorhexidine gluconate 3.15% w/v

Isopropyl alcohol 70% v/v

Purposes

Antiseptic

Antiseptic

Use

for the preparation of the patient's skin prior to surgery or injection

Warnings

- For external use only
- Flammable, keep away from fire or flame
- Do not use with electrocautery procedures

Allergy alert

This product may cause a severe allergic reaction. Symptoms may include:

- wheezing/difficulty breathing
- shock
- facial swelling
- hives
- rash

If an allergic reaction occurs, stop use and seek medical help right away.

Do not use

- on patients allergic to chlorhexidine gluconate or any other ingredient in this product
- for lumbar puncture or in contact with the meninges
- on open skin wounds or as a general skin cleanser
- under occlusive patch

When using this product

keep out of eyes, ears, mouth and mucous membranes. May cause serious or permanent injury if permitted to enter and remain.

If contact occurs, rinse with cold water right away and contact a doctor.

Stop use and ask a doctor if

irritation, sensitization, or allergic reaction occurs. These may be signs of a serious condition.

Keep out of reach of children.

If swallowed, get medical help or contact a Poison Control Center right away.

Directions

- use with care in premature infants or infants under 2 months of age. These products may cause irritation or chemical burns.
- maximum treatment area for one maxi swabstick is approximately: dry site: 4 by 4 inches (10 by 10 cm) or moist site: 3 by 5 inches (7.5 by 12.5 cm)
- tear open the pouch to expose the swabstick
- remove the swabstick from package. Do not touch the foam tip.
- prior to surgery or injection, apply one flat side of foam tip to the proposed skin site and prep the skin in vigorous back-and-forth repeated strokes, turning the swabstick over (unused side of the foam tip) half way in the procedure
- dry site: scrub repeatedly back and forth for 15 seconds with each side of the applicator for a total of 30 seconds. Allow to air dry for approximately 30 seconds.
- moist site: scrub repeatedly back and forth for 1 minute with each side of the applicator for a total of 2 minutes. Allow to air dry for approximately 1.5 minutes.
- do not blot or wipe dry
- discard after a single use

Other information

- store between 68-77°F (20-25°C)
- avoid freezing and excessive heat above 104°F (40°C)
- for hospital and professional use only

Inactive ingredients

USP purified water

Package/Label Principal Display Panel

Packet Label

Box Label

Packet (bulk)

Insert